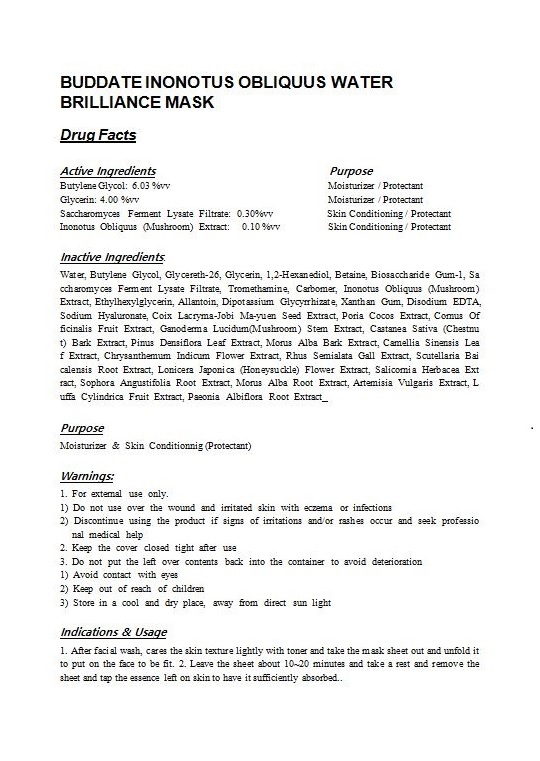 DRUG LABEL: BUDDATE INONOTUS OBLIQUUS WATER BRILLIANCE MASK
NDC: 71173-1000 | Form: LIQUID
Manufacturer: BUDDATE Co Ltd
Category: otc | Type: HUMAN OTC DRUG LABEL
Date: 20251130

ACTIVE INGREDIENTS: BUTYLENE GLYCOL 6.03 g/100 g; INONOTUS OBLIQUUS FRUITING BODY 0.1 g/100 g; GLYCERIN 4 g/100 g
INACTIVE INGREDIENTS: WATER

Drug Facts

ACTIVE INGREDIENT

Butylene Glycol: 6.03 %vv

Glycerin: 4.00 %vv

Inonotus Obliquus (Mushroom) Extract: 0.10 %vv

INACTIVE INGREDIENT

Water, Glycereth-26, 1,2-Hexanediol, Betaine, Biosaccharide Gum-1, Saccharomyces Ferment Lysate Filtrate, Tromethamine, Carbomer, Ethylhexylglycerin, Allantoin, Dipotassium Glycyrrhizate, Xanthan Gum, Disodium EDTA, Sodium Hyaluronate, Coix Lacryma-Jobi Ma-yuen Seed Extract, Poria Cocos Extract, Cornus Officinalis Fruit Extract, Ganoderma Lucidum(Mushroom) Stem Extract, Castanea Sativa (Chestnut) Bark Extract, Pinus Densiflora Leaf Extract, Morus Alba Bark Extract, Camellia Sinensis Leaf Extract, Chrysanthemum Indicum Flower Extract, Rhus Semialata Gall Extract, Scutellaria Baicalensis Root Extract, Lonicera Japonica (Honeysuckle) Flower Extract, Salicornia Herbacea Extract, Sophora Angustifolia Root Extract, Morus Alba Root Extract, Artemisia Vulgaris Extract, Luffa Cylindrica Fruit Extract, Paeonia Albiflora Root Extract

PURPOSE

Moisturizer & Skin Conditionnig (Protectant)

keep out of reach of the children

INDICATIONS AND USAGE

1. After facial wash, cares the skin texture lightly with toner and take the mask sheet out and unfold it to put on the face to be fit.

2. Leave the sheet about 10~20 minutes and take a rest and remove the sheet and tap the essence left on skin to have it sufficiently absorbed..

WARNINGS

1. For external use only.

1) Do not use over the wound and irritated skin with eczema or infections

2) Discontinue using the product if signs of irritations and/or rashes occur and seek professional medical help

2. Keep the cover closed tight after use

3. Do not put the left over contents back into the container to avoid deterioration

1) Avoid contact with eyes

2) Keep out of reach of children

3) Store in a cool and dry place, away from direct sun light

DOSAGE AND ADMINISTRATION

for external use only